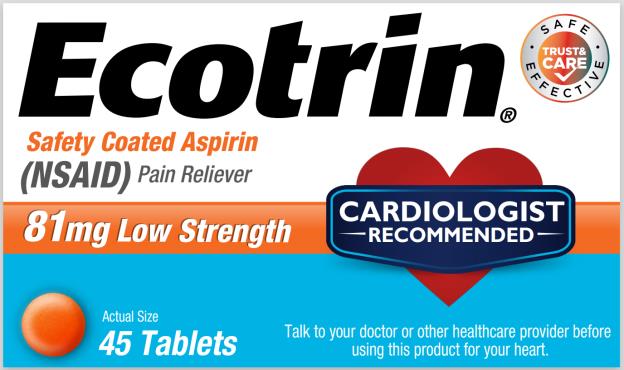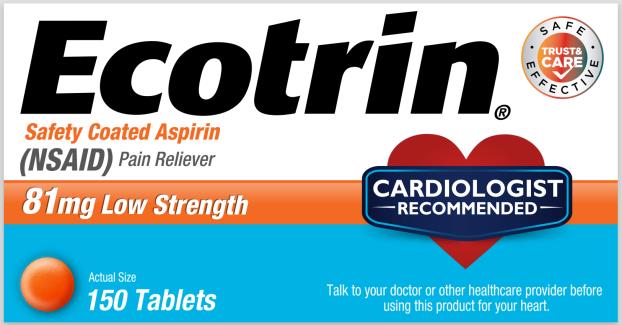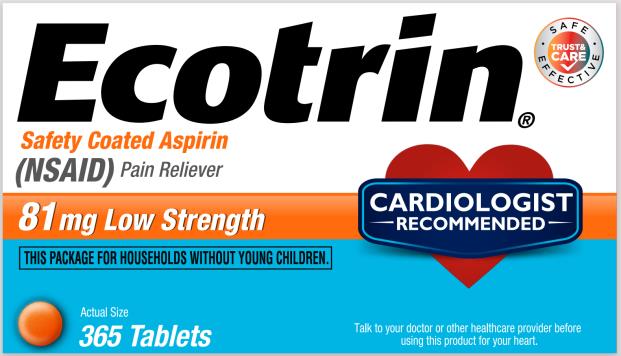 DRUG LABEL: Ecotrin
NDC: 63029-311 | Form: TABLET, COATED
Manufacturer: Medtech Products Inc.
Category: otc | Type: HUMAN OTC DRUG LABEL
Date: 20250116

ACTIVE INGREDIENTS: ASPIRIN 81 mg/1 1
INACTIVE INGREDIENTS: FERROSOFERRIC OXIDE; SILICON DIOXIDE; STARCH, CORN; CROSCARMELLOSE SODIUM; D&C YELLOW NO. 10; FD&C YELLOW NO. 6; HYPROMELLOSES; CELLULOSE, MICROCRYSTALLINE; POLYDEXTROSE; POLYETHYLENE GLYCOL, UNSPECIFIED; Polyvinyl Acetate Phthalate; PROPYLENE GLYCOL; SODIUM ALGINATE; SODIUM BICARBONATE; STEARIC ACID; TALC; TITANIUM DIOXIDE; TRIACETIN; TRIETHYL CITRATE

Ecotrin Low Strength

Drug Facts

Active ingredient

(in each tablet)

Aspirin (NSAID) *81mg

*nonsteroidal anti-inflammatory drug

Purpose

Pain reliever

Uses

- temporarily relieves minor aches and pain due to:
  - headache
  - minor arthritis pain
  - toothache
  - muscle pain
  - menstrual pain
  - colds
- or as recommended by your doctor

Warnings

Reye’s syndrome: Children and teenagers who have or are recovering from chicken pox or flu-like symptoms should not use this product. When using this product, if changes in behavior with nausea and vomiting occur, consult a doctor because these symptoms could be an early sign of Reye’s syndrome, a rare but serious illness.

Allergy alert: Aspirin may cause a severe allergic reaction which may include:

- hives
- facial swelling
- shock
- asthma (wheezing)

Stomach bleeding warning: This product contains an NSAID, which may cause severe stomach bleeding. The chance is higher if you

- are age 60 or older
- take more or for a longer time than directed
- have had stomach ulcers or bleeding problems
- take a blood thinning (anticoagulant) or steroid drug
- take other drugs containing prescription or nonprescription NSAIDs (aspirin, ibuprofen, naproxen, or others)
- have 3 or more alcoholic drinks every day while using this product

Do not use

if you have ever had an allergic reaction to aspirin or any other pain reliever/fever reducer.

Ask a doctor before use if

- stomach bleeding warning applies to you
- you have a history of stomach problems, such as heartburn
- you have asthma
- you have high blood pressure, heart disease, liver cirrhosis, or kidney disease
- you are taking a diuretic

Ask a doctor or pharmacist before use if you are

taking a prescription drug for ▪ gout ▪ diabetes ▪arthritis

Stop use and ask a doctor if

- you experience any of the following signs of stomach bleeding:
  - feel faint
  - vomit blood
  - have bloody or black stools
  - have stomach pain that does not get better
- an allergic reaction occurs. Seek medical help right away.
- any new symptoms appear
- ringing in the ears or a loss of hearing occurs.
- pain gets worse or lasts more than 10 days
- redness or swelling is present.

These could be signs of a serious condition.

If pregnant or breast-feeding,

ask a health professional before use. It is especially important not to use aspirin at 20 weeks or later in pregnancy unless definitely directed to do so by a doctor because it may cause problems in the unborn child or complications during delivery.

Keep out of reach of children.

In case of overdose, get medical help or contact a Poison Control Center (1-800-222-1222) right away.

Directions

- drink a full glass of water with each dose
- adults and children 12 years and over: take 4 to 8 tablets every 4 hours, not to exceed 48 tablets in 24 hours unless directed by a doctorchildren under 12 years: do not use unless directed by a doctor

Other information

- store at 25°C (77°F); exclusions permitted between 15°C-30°C (59°F-86°F)
- see end flap for expiration date and lot number
- avoid excessive heat and humidity

Inactive ingredients

black iron oxide, colloidal silicon dioxide, corn starch, croscarmellose sodium, D&C yellow #10 aluminum lake, FD&C yellow #6 aluminum lake, hypromellose, microcrystalline cellulose, polydextrose, polyethylene glycol, polyvinyl acetate phthalate, propylene glycol, shellac wax, simethicone, sodium alginate, sodium bicarbonate, stearic acid, talc, titanium dioxide, triacetin, triethyl citrate

Questions or comments?

1-866-255-5202 Ecotrin.com

PRINCIPAL DISPLAY PANEL

Ecotrin®
Safety Coated Aspirin (NSAID) Pain Reliever
81 mg Low Strength

45 Tablets

PRINCIPAL DISPLAY PANEL

Ecotrin®
Safety Coated Aspirin (NSAID) Pain Reliever
81 mg Low Strength

150 Tablets

PRINCIPAL DISPLAY PANEL

Ecotrin®
Safety Coated Aspirin (NSAID) Pain Reliever
81 mg Low Strength

365 Tablets